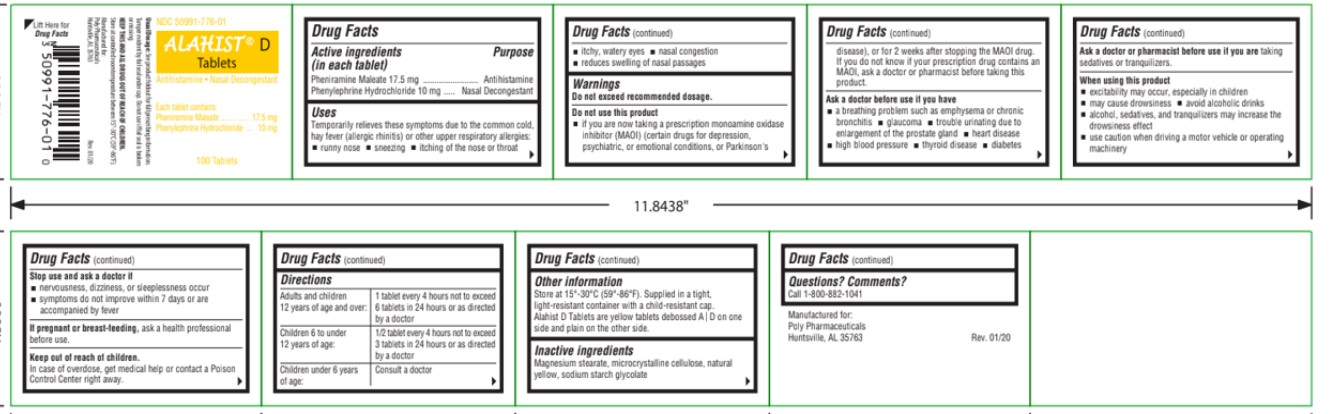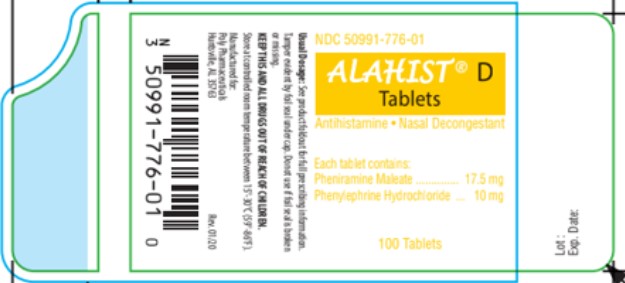 DRUG LABEL: Alahist D
NDC: 50991-776 | Form: TABLET
Manufacturer: Poly Pharmaceuticals, Inc.
Category: otc | Type: HUMAN OTC DRUG LABEL
Date: 20251203

ACTIVE INGREDIENTS: PHENIRAMINE MALEATE 17.5 mg/1 1; PHENYLEPHRINE HYDROCHLORIDE 10 mg/1 1
INACTIVE INGREDIENTS: MAGNESIUM STEARATE; MICROCRYSTALLINE CELLULOSE; FERRIC OXIDE YELLOW; SODIUM STARCH GLYCOLATE TYPE A CORN

Alahist D

ACTIVE INGREDIENT

Active Ingredient (in each tablet) Purpose

Pheniramine Maleate 17mg | Antihistamine
Phenylephrine HCl 10mg | Nasal Decongestant

USES

Temporarily relieves these symptoms due to the
common cold, hay fever (allergic rhinitis) or other
upper respiratory allergies:

-  runny nose
-  sneezing
-  itching of the nose or throat
-  itchy, watery eyes
-  nasal congestion 
  - reduces swelling of nasal passages

WARNINGS

Do not exceed recommended dosage.

Do not use this product
 if you are now taking a prescription monoamine oxidase inhibitor (MAOI) (certain drugs for depression, psychiatric, or
emotional conditions, or Parkinson's disease), or for 2 weeks after stopping the MAOI drug. If you do not know if your prescription drug contains an MAOI, ask a doctor or pharmacist before taking this product.

Ask a doctor before use ifyou have

-  a breathing problem such as emphysema or chronic bronchitis
-  glaucoma
-  trouble urinating due to enlargement of the prostate gland
-  heart disease
-  high blood pressure
-  thyroid disease 
- diabetes

Ask a doctor or pharmacist before use if you are taking sedatives or tranquilizers.

When using this product

-  excitability may occur, especially in children
-  may cause drowsiness
-  avoid alcoholic drinks
-  alcohol, sedatives, and tranquilizers may increase the drowsiness effect
-  use caution when driving a motor vehicle or operating machinery

Stop use and ask a doctor if
 nervousness, dizziness, or sleeplessness occur
 symptoms do not improve within 7 days or are accompanied by fever

If pregnant or breast-feeding, ask a health
professional before use.

DIRECTIONS

Adults and children 12 years of age and over | 1 tablet every 4 hours, not to exceed 6 tablets in 24 hours
Children 6 to under 12 years of age; Children under 6 consult a doctor | 1/2 tablet every 4 hours, not to exceed 3 tablets in 24 hours

INACTIVE INGREDIENTS

Magnesium Stearate, Microcrystalline Cellulose, Natural Yellow, Sodium Starch Glycolate

QUESTIONS

Questions? Comments?
Call 1-800-882-1041
Manufactured for:
Poly Pharmaceuticals
Huntsville, AL 35763 Rev. 04/17

OTHER INFORMATION

Store at 15°-30°C (59°-86°F). Supplied in a tight, light-resistant container with a child-resistant cap. Alahist D Tablets are yellow,debossed "A" bisect "D" on one side and plain on the other.

Keep out of reach of children

In case of overdose, get medical help or contact a Poison Control Center right away.

PURPOSE

Antihistamine

Nasal Decongestant